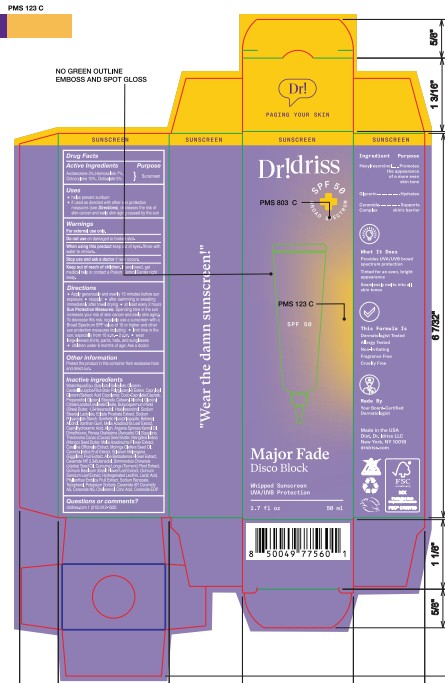 DRUG LABEL: Dr. Idriss Major Fade Disco Block Whipped Sunscreen SPF 50
NDC: 85246-100 | Form: LOTION
Manufacturer: PILLOWTALKDERM LLC
Category: otc | Type: HUMAN OTC DRUG LABEL
Date: 20251111

ACTIVE INGREDIENTS: OCTISALATE 5 g/100 mL; OCTOCRYLENE 10 g/100 mL; AVOBENZONE 3 g/100 mL; HOMOSALATE 7 g/100 mL
INACTIVE INGREDIENTS: BUTYROSPERMUM PARKII (SHEA) BUTTER; ALOE BARBADENSIS LEAF; HYDROGENATED SOYBEAN LECITHIN; PROPANEDIOL; BUTYLOCTYL SALICYLATE; GLYCERIN; EUPHORBIA CERIFERA (CANDELILLA) WAX; COCO-CAPRYLATE/CAPRATE; GLYCERYL STEARATE; 1,2-HEXANEDIOL; SODIUM STEAROYL LACTYLATE; CERAMIDE NP; SIMMONDSIA CHINENSIS (JOJOBA) SEED OIL; CERAMIDE NS; POTASSIUM SORBATE; COCCINIA GRANDIS FRUIT; CETEARYL ALCOHOL; THEOBROMA CACAO (COCOA) SEED BUTTER; LACTIC ACID; CHOLESTEROL; SQUALANE; SODIUM POLYACRYLATE STARCH (12 MICROMETER PARTICLE); ALGIN; SODIUM BENZOATE; CERAMIDE 4; CITRIC ACID; SIMMONDSIA CHINENSIS SEED WAX; 2,3-BUTANEDIOL; WATER; XANTHAN GUM; TOCOPHEROL; GLYCERYL CITRATE/LACTATE/LINOLEATE/OLEATE; HEXYLRESORCINOL; ECLIPTA PROSTRATA WHOLE; CERAMIDE AP; CERAMIDE 1; ORYZA SATIVA (RICE) BRAN; MORINGA OLEIFERA SEED OIL; SOLANUM MELONGENA WHOLE; CURCUMA LONGA (TURMERIC) ROOT POWDER; MANGIFERA INDICA SEED BUTTER; ARGANIA SPINOSA KERNEL OIL; PERSEA GRATISSIMA (AVOCADO) OIL; DIMETHICONE; MICA; CAPRYLOYL GLYCERIN/SEBACIC ACID COPOLYMER (2000 MPA.S); CAPRYLHYDROXAMIC ACID; BEHENYL ALCOHOL; CORALLINA OFFICINALIS; OCIMUM TENUIFLORUM LEAF OIL; PHYLLANTHUS EMBLICA FRUIT JUICE; POLYGLYCERIN-3; MELIA AZADIRACHTA LEAF; OCIMUM BASILICUM (BASIL) LEAF

Dr. Idriss Major Fade Disco Block Whipped Sunscreen SPF 50 (85246-100)

Drug Facts

ACTIVE INGREDIENT

Active Ingredients | Purpose
Avobenzone 3% | Sunscreen
Homosalate 7% | Sunscreen
Octocrylene 10% | Sunscreen
Octisalate 5% | Sunscreen

Uses

- helps prevent sunburn
- if used as directed with other sun protection measures (see Directions), decreases the risk of skin cancer and early skin aging caused by the sun

WARNINGS

For external use only.

Do not use on damaged or broken skin

When using this product keep out of eyes. Rinse with water to remove.

STOP USE

Stop uses and ask a doctor if rash occurs.

Keep out of reach of children. If swallowed, get medical help or contact a Poison Control Center right away.

Directions

- Apply generously and evenly 15 minutes before sun exposure

Reapply:

- After swimming or sweating immediately after towel drying
- At least every 2 hours

Sun Protection Measures: Spending time in the sun increases your risk of skin cancer and early skin aging. To decrease this risk, regularly use a sunscreen with a Broad Spectrum SPF value of 15 or higher and other sun protection measures including:

- limit time in the sun, especially from 10 a.m. - 2 p.m.
- wear long-sleeved shirts, pants, hates, and sunglasses
- children under 6 months of age: Ask a doctor

OTHER SAFETY INFORMATION

Protect the product in this container from excessive heat and direct sun.

INACTIVE INGREDIENT

Water/Aqua/Eau, Butyloctyl Salicylate, Glycerin, Candelilla/Jojoba/Rice Bran Polyglyceryl-3 Esters, Capryloyl Glycerin/Sebacic Acid Copolymer, Coco-Caprylate/Caprate, Propanediol, Glyceryl Stearate, Cetearyl Alcohol, Glyceryl Citrate/Lactate/Linoleate/Oleate, Butyrospermum Parkii (Shea) Butter, 1,2-Hexanediol, Hexylresorcinol, Sodium Stearoyl Lactylate, Edipta Prostrata Extract, Sodium Polyacrylate Starch, Synthetic Fluorphlogopite, Behenyl Alcohol, Xanthan Gum, Melia Azadirachta Leaf Extract, Caprylhydroxamic Acid, Algin, Argania Spinosa Kernel Oil, Dimethicone, Persea Gratissima (Avocado) Oil, Squalane, Theobroma Cacao (Cocoa) Seed Butter, Mangifera Indica (Mango) Seed Butter, Melia Azadirachta Flower Extract, Corallina Officinalis Extract, Moringa Oleifera Seed Oil, Coccinia Indica Fruit Extract, Aloe Barbadensis Flower Extract, Ceramide NP, 2,3-Butanediol, Simmondsia Chinensis (Jojoba) Seed Oil, Curcuma Longa (Turmeric) Root Extract, Ocimum Basilicum (Basil) Flower/Leaf Extract, Ocimum Sanctum Leaf Extract, Hydrogenated Lecithin, Lactic Acid, Phyllanthus Emblica Fruit Extract, Sodium Benzoate, Tocopherol, Potassium Sorbate, Ceramide AP, Cermaide AS, Ceramide NS, Cholesterol, Citric Acid, Ceramide EOP

Questions or Comments?

dridriss.com 1 (212) 612-1520

Dr. Idriss Major Fade Disco Block SPF 50

Dr. Idriss

SPF 50 Broad Spectrum

Major Fade

Disco Block

Whipped Sunscreen

UVA/UVB Protection

1.7 fl oz 50 mL